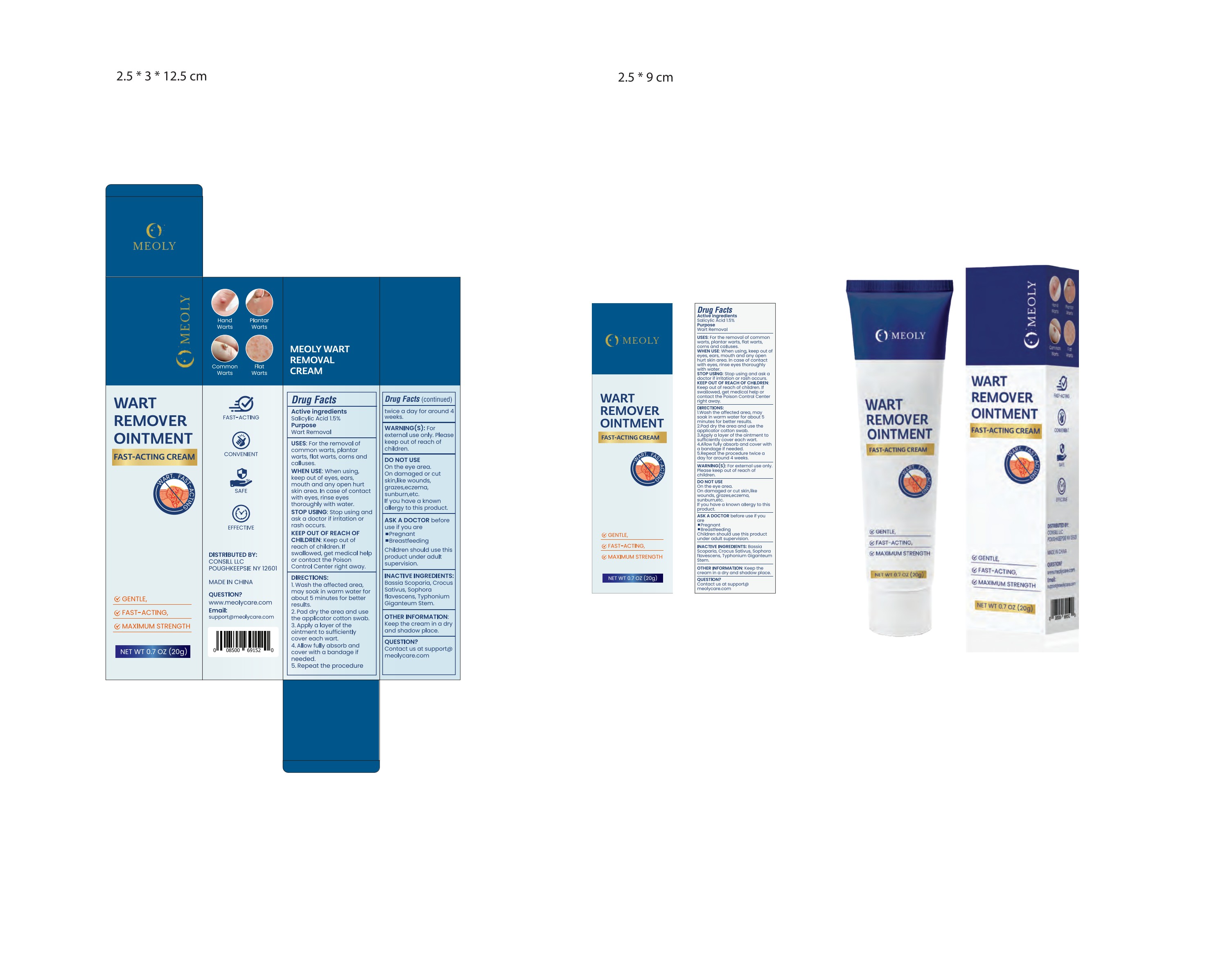 DRUG LABEL: MEOLY Wart Removal Cream 20g
NDC: 83818-008 | Form: OINTMENT
Manufacturer: Shenzhen Xinxin Yunhai Technology Co., Ltd.
Category: otc | Type: HUMAN OTC DRUG LABEL
Date: 20241216

ACTIVE INGREDIENTS: SALICYLIC ACID 1.5 g/100 g
INACTIVE INGREDIENTS: SOPHORA FLAVESCENS ROOT; TYPHA ANGUSTIFOLIA STEM; BASSIA SCOPARIA WHOLE; SAFFRON

83818-008

Active Ingredient

Salicylic Acid 1.5%

Purpose

Wart Removal

Use

For the removal of common warts, plantar warts, flat warts, corns, and calluses.

Warnings

For external use only. Please keep out of reach of children.

Do not use

On the eye area. On damaged or cut skin, like wounds, grazes, eczema, sunburn, etc. If you have a known allergy to this product.

When Using

Keep out of eyes, ears, mouth, and any open hurt skin area. In case of contact with eyes, rinse eyes thoroughly with water.

Stop Use

Stop using and ask a doctor if irritation or rash occurs.

Ask Doctor

stop using andask a doctor if irritation orrash occurs.

Keep out of reach of children. If swallowed, get medical help or contact the Poison Control Center right away.

Directions

1. Wash the affected area, may soak in warm water for about 5 minutes for better results.
2. Pat dry the area and use the applicator cotton swab.
3. Apply a layer of the ointment to sufficiently cover each wart.
4. Allow fully absorb and cover with a bandage if needed.
5. Repeat the procedure twice a day for around 4 weeks.

Other information

Keep the cream in a dry and shaded place.

Inactive ingredients

Bassia Scoparia, Crocus Sativus, Sophora Flavescens, Typhonium Giganteum Stem.

Questions

Contact us at support@meolycare.com